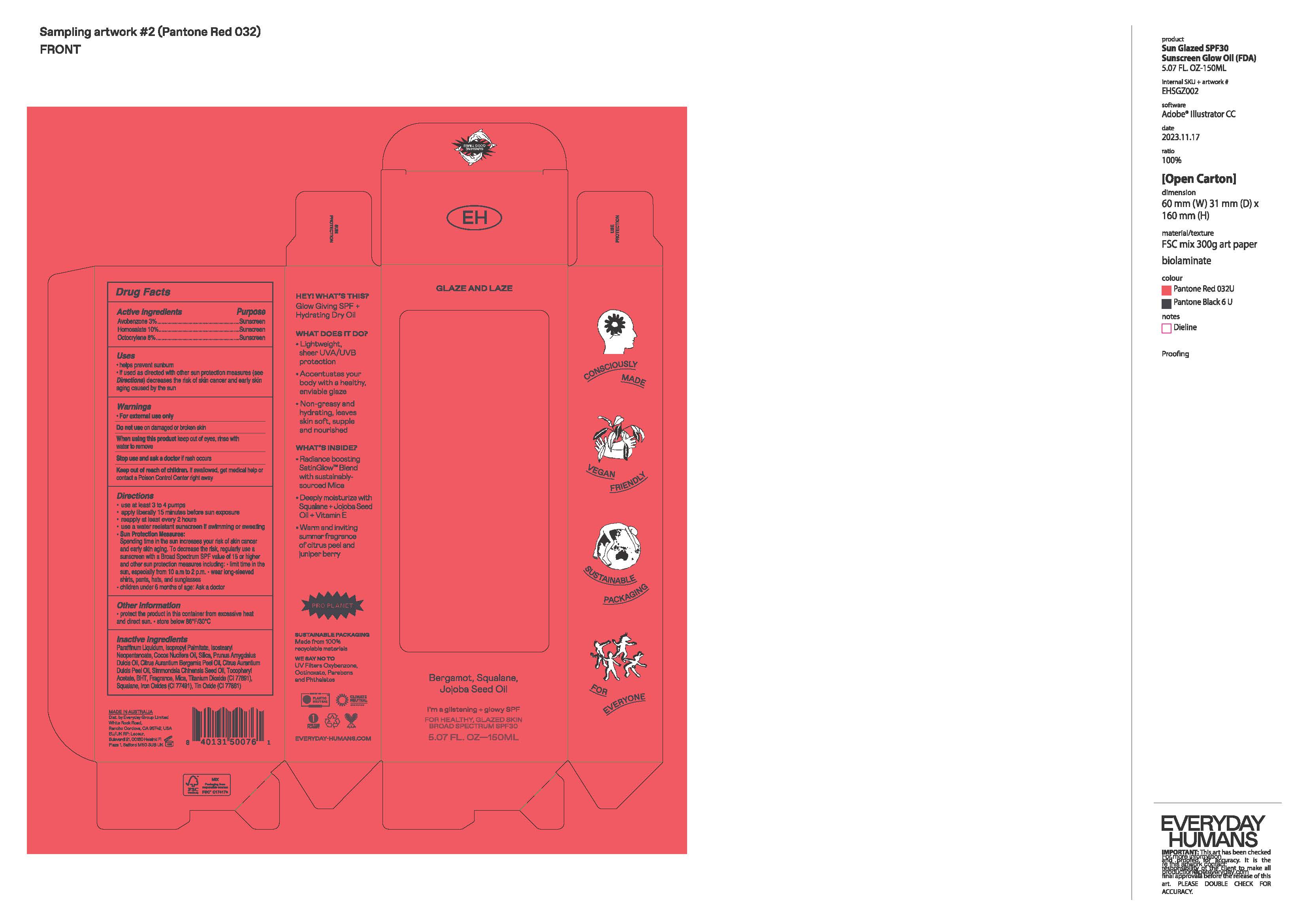 DRUG LABEL: Sun Glazed SPF 30 Sunscreen Glow Oil
NDC: 70157-034 | Form: OIL
Manufacturer: Baxter Laboratories Pty. Ltd.
Category: otc | Type: HUMAN OTC DRUG LABEL
Date: 20250925

ACTIVE INGREDIENTS: HOMOSALATE 10 g/100 mL; OCTOCRYLENE 8 g/100 mL; AVOBENZONE 3 g/100 mL
INACTIVE INGREDIENTS: ISOSTEARYL NEOPENTANOATE; ISOPROPYL PALMITATE; BHT; TITANIUM DIOXIDE; PRUNUS AMYGDALUS DULCIS (SWEET ALMOND) OIL; SQUALANE; ORANGE OIL; COCONUT OIL; TIN OXIDE; BERGAMOT OIL; SILICON DIOXIDE; PARAFFINUM LIQUIDUM; CI 77491; MICA; SIMMONDSIA CHINENSIS (JOJOBA) SEED OIL; .ALPHA.-TOCOPHEROL ACETATE

Sun Glazed SPF 30 Sunscreen Glow Oil

Active ingredients Purpose

Avobenzone 3% ...Sunscreen

Homosalate 10%...Sunscreen

Octocrylene 8%.....Sunscreen

Uses

- helps prevent sunburn
- If used as directed with other sun protection measures (see Directions) decreases the risk of skin cancer and early skin aging caused by the sun.

Keep out of reach of children. If swallowed, get medical help or contact a Poison Control Center right away.

Stop use and ask a doctor if rash occurs.

Warnings

- For external use only

Do not use on damaged or broken skin

When using this product keep out of eyes, rinse with water to remove

Directions

- Use at least 3 to 4 pumps
- Apply liberally 15 minutes before sun exposure
- Reapply at least every 2 hours
- use a water resistant sunscreen if swimming or sweating

- Sun Protection Measures:

Spending time in the sun increases your risk of skin cancer and early skin aging. To decrease this risk, regularly use a sunscreen with a Broad Spectrum SPF value of 15 or higher and other sub and other sun protection measures including:

- Limit time in the sun, especially from 10 a.m.- 2 p.m.
- Wear long-sleeved shirts, pants, hats and sunglasses
- Children under 6 months: Ask a doctor

Inactive ingredients

Paraffinum Liquidum, Isopropyl Palmitate, Isostearyl Neopentanoate, Cocos Nucifera Oil, Silica, Prunus Amygdalus Dulcis Oil, Citrus Aurantium Dulcis Peel Oil, Simmondsia Chinensis Seed Oil, Tocopheryl Acetate, BHT, Fragrance, Mica, Titanium Dioxide (CI 77891), Squalane, Iron Oxides (CI 77491), Tin Oxide (CI 77861)

PACKAGE LABEL

Glaze and Laze

I'm a glistening + glowy SPF

Broad Spectrum SPF30

5.07 FL. OZ - 150ML